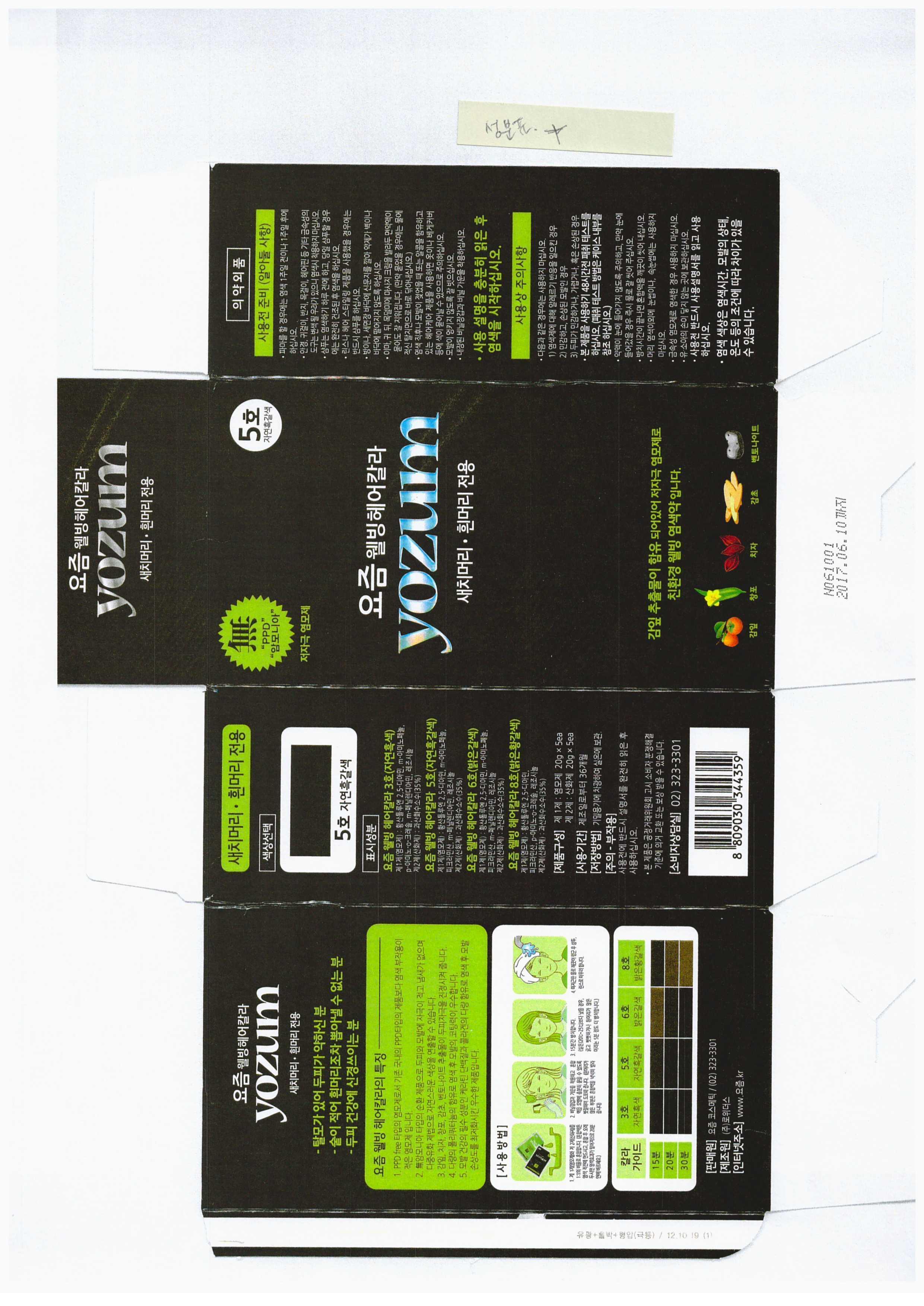 DRUG LABEL: YOZUM WELL BEING HAIR COLOR
NDC: 69525-2001 | Form: LIQUID
Manufacturer: YOZUM KOREA 
Category: otc | Type: HUMAN OTC DRUG LABEL
Date: 20150111

ACTIVE INGREDIENTS: DEXPANTHENOL 0.2 g/100 g
INACTIVE INGREDIENTS: WATER; ASCORBIC ACID; CITRIC ACID MONOHYDRATE

Drug Facts

ACTIVE INGREDIENT

PANTHENOL

INACTIVE INGREDIENT

water, ascorbic acid, citric acid, mineral, cetearyl alcohol etc

PURPOSE

hair dyeing

keep out of reach of the children

INDICATIONS AND USAGE

add 1st pouch to 2nd pouch and mix well
apply the mixture evenly to hair
after 15 minutes, rinse out with war water and wash hair with shampoo or soap
rinse until the water runs clear
increase or decrease the amount of mixture depending on length/thickness of hair

WARNINGS

keep in a cool place do not store in high temperature condition

DOSAGE AND ADMINISTRATION

for external use only